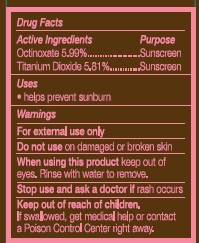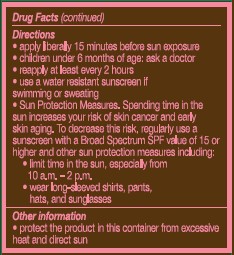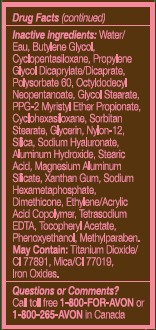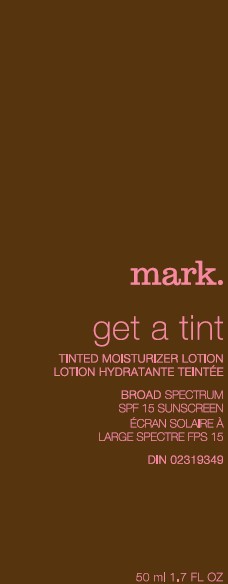 DRUG LABEL: mark. get a tint
NDC: 10096-0173 | Form: LOTION
Manufacturer: Avon Products, Inc.
Category: otc | Type: HUMAN OTC DRUG LABEL
Date: 20120523

ACTIVE INGREDIENTS: OCTINOXATE	 2.995 mL/50 mL; TITANIUM DIOXIDE	 2.905 mL/50 mL

Drug Facts

Active Ingredients
Octinoxate 5.99%.........
Titanium Dioxide 5.81%...

Purpose
..... Sunscreen

..... Sunscreen

Uses
■ helps prevent sunburn

WARNINGS
For external use only

Do not use on damaged or broken skin

When using this product keep out of eyes. Rinse with water to remove.

Stop use and ask a doctor if rash occurs

Keep out of reach of children. If swallowed, get medical help or contact a Poison Control Center right away.

Directions
• apply liberally 15 minutes before sun exposure
• children under 6 months of age: ask a doctor
• reapply at least every 2 hours
• use a water resistant sunscreen if swimming or sweating

• Sun Protection Measures. Spending time in the sun increases your risk of skin cancer and early skin aging. To decrease this risk, regularly use a sunscreen with a Broad Spectrum SPF value of 15 or higher and other sun protection measures including:
• limit time in the sun, especially from 10 a.m. – 2 p.m.
• wear long-sleeved shirts, pants, hats, and sunglasses

Other Information
■ protect the product in this container from excessive heat and direct sun.

Inactive ingredients:

WATER/EAU
BUTYLENE GLYCOL
CYCLOPENTASILOXANE
PROPYLENE GLYCOL DICAPRYLATE/DICAPRATE
POLYSORBATE 60
OCTYLDODECYL NEOPENTANOATE
GLYCOL STEARATE
PPG-2 MYRISTYL ETHER PROPIONATE
CYCLOHEXASILOXANE
SORBITAN STEARATE
GLYCERIN
NYLON-12
SILICA
ALUMINUM HYDROXIDE
STEARIC ACID
MAGNESIUM ALUMINUM SILICATE
XANTHAN GUM
SODIUM HEXAMETAPHOSPHATE
DIMETHICONE
ETHYLENE/ACRYLIC ACID COPOLYMER
SODIUM HYALURONATE
TOCOPHERYL ACETATE
TETRASODIUM EDTA
PHENOXYETHANOL
METHYLPARABEN
MAY CONTAIN:
TITANIUM DIOXIDE/CI 77891
IRON OXIDES
MICA/CI 77019

Questions or Comments? Call toll free 1-800-FOR-AVON or 1-800-265-AVON in Canada